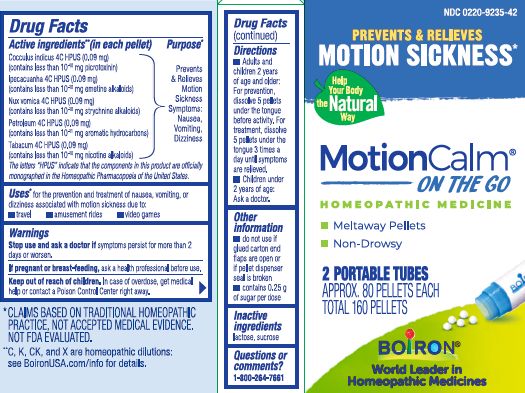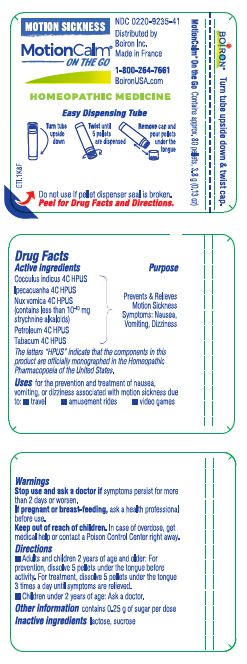 DRUG LABEL: MotionCalm
NDC: 0220-9235 | Form: PELLET
Manufacturer: Boiron
Category: homeopathic | Type: HUMAN OTC DRUG LABEL
Date: 20240801

ACTIVE INGREDIENTS: IPECAC 4 [hp_C]/1 1; ANAMIRTA COCCULUS SEED 4 [hp_C]/1 1; STRYCHNOS NUX-VOMICA SEED 4 [hp_C]/1 1; TOBACCO LEAF 4 [hp_C]/1 1; KEROSENE 4 [hp_C]/1 1
INACTIVE INGREDIENTS: SUCROSE; LACTOSE, UNSPECIFIED FORM

MotionCalm Pellets

Active ingredients**

Cocculus indicus 4C HPUS (0.9 mg) (contains less than 10-10 mg picrotoxinin)

Ipecacuanha 4C HPUS (0.9 mg) (contains less than 10-10 mg emetine alkaloids)

Nux vomica 4C HPUS (0.9 mg) (contains less than 10-10 mg strychnine alkaloids)

Petroleum 4C HPUS (0.9 mg) (contains less than 10-11 mg aromatic hydrocarbons)

Tabacum 4C HPUS (0.9 mg) (contains less than 10-10 mg nicotine alkaloids)

The letters "HPUS" indicate that the components in this product are officially monographed in the Homeopathic Pharmacopoeia of the United States.

Purpose*

Prevents & Relieves Motion Sickness Symptoms: Nausea, Vomiting, Dizziness

Uses*

for prevention and treatment of nausea, vomiting, or dizziness associated with motion sickness due to:

- travel
- amusement rides
- video games

Stop use and ask a doctor if symptoms persist for more than 2 days or worsen.

PREGNANCY OR BREAST FEEDING

If pregnant or breast-feeding, ask a health professional before use.

Keep out of reach of children. In case of accidental overdose, get medical help or contact a Poison Control Center right away.

DOSAGE AND ADMINISTRATION

- Adults and children 2 years of age and older: For prevention, dissolve 5 pellets under the tongue before activity. For treatment, dissolve 5 pellets under the tongue 3 times a day until symptoms are relieved.
- Children under 2 years of age: Ask a doctor.

INACTIVE INGREDIENT

lactose, sucrose

QUESTIONS

1-800-264-7661

Distributed by Boiron, Inc.

Newtown Square, PA

19073

- do not use if glued carton end flaps are open or if pellet dispenser seal is broken
- contains 0.25g of sugar per dose

2 PORTABLE TUBES

APPROX. 80 PELLETS EACH

TOTAL 160 PELLETS

PREVENTS & RELIEVES

MOTION SICKNESS*

*CLAIMS BASED ON TRADITIONAL HOMEOPATHIC PRACTICE, NOT ACCEPTED MEDICAL EVIDENCE. NOT FDA EVALUATED.
**C,K,CK, and X are homeopathic dilutions: see BoironUSA.com/info for details.